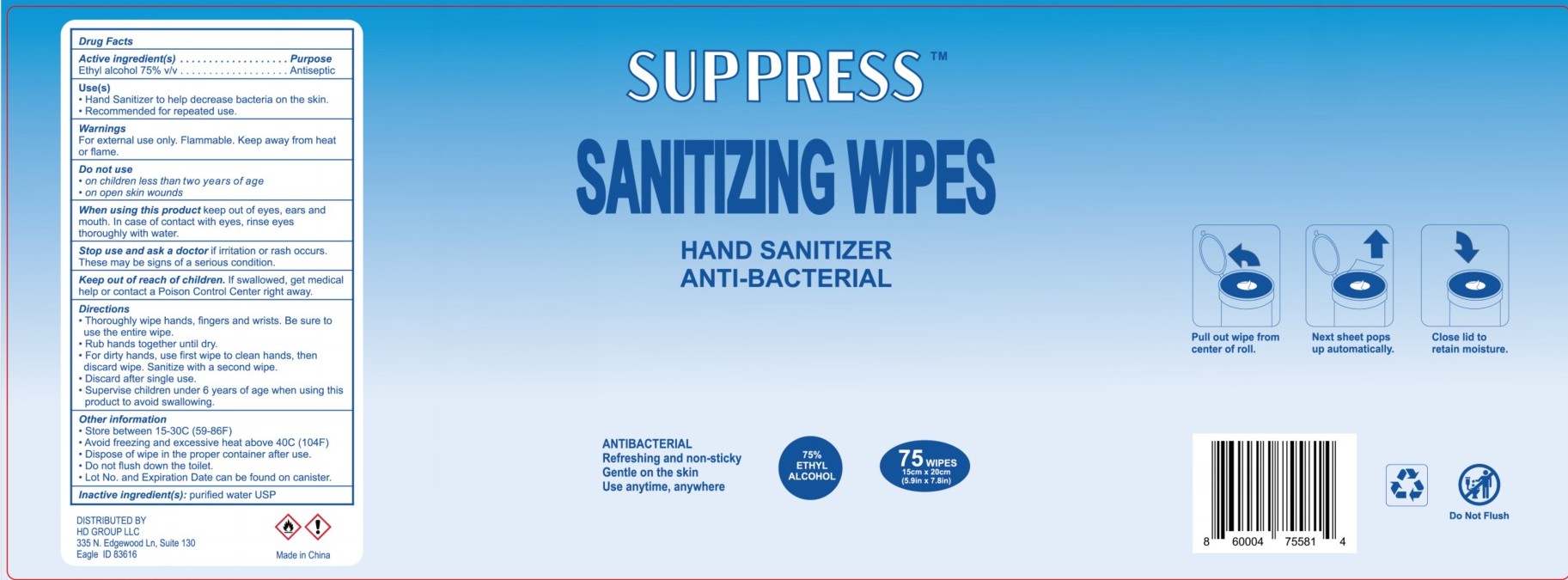 DRUG LABEL: Suppress Sanitizing Wipes
NDC: 74913-611 | Form: CLOTH
Manufacturer: SHANTOU S.E.Z BAOJIE INDUSTRY CO., LTD
Category: otc | Type: HUMAN OTC DRUG LABEL
Date: 20200806

ACTIVE INGREDIENTS: ALCOHOL 75 mL/100 mL
INACTIVE INGREDIENTS: WATER 25 mL/100 mL

Suppress Sanitizing Wipes

Stop use and ask a doctor

If irritation or rash occurs. These may be signs of a serious condition.

Do not use

On Children less than two years of age

On open skin wounds

Directions

Thoroughly wipe hands, fingers and wrists. Be sure to use the entire wipe

Rub hands together until dry

For dirty hands use first wipe to clean hands then discard wipe.Sanitize with a second wipe

Discard after single use

Supervise children under 6 years of age when using this product to avoid swallowing.

Keep out of reach of children

If swallowed, get medical help or contact a poison control center right aways.

Active ingredient

Ethyl alcohol 75%

Use(s)

Hand sanitizer to help decrease bacteria on the skin.

Recommended for repeated use.

Antiseptic, alcohol wipes